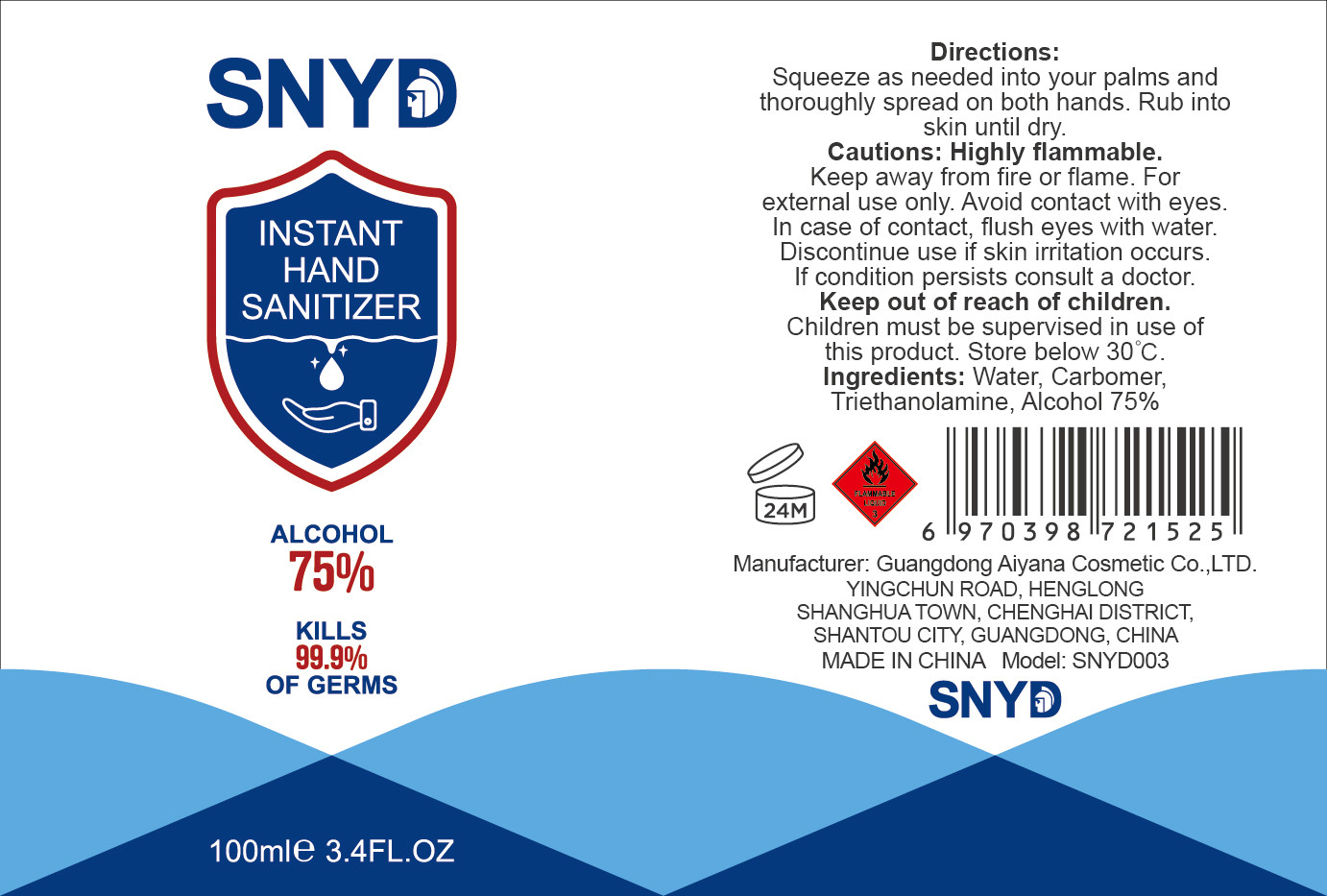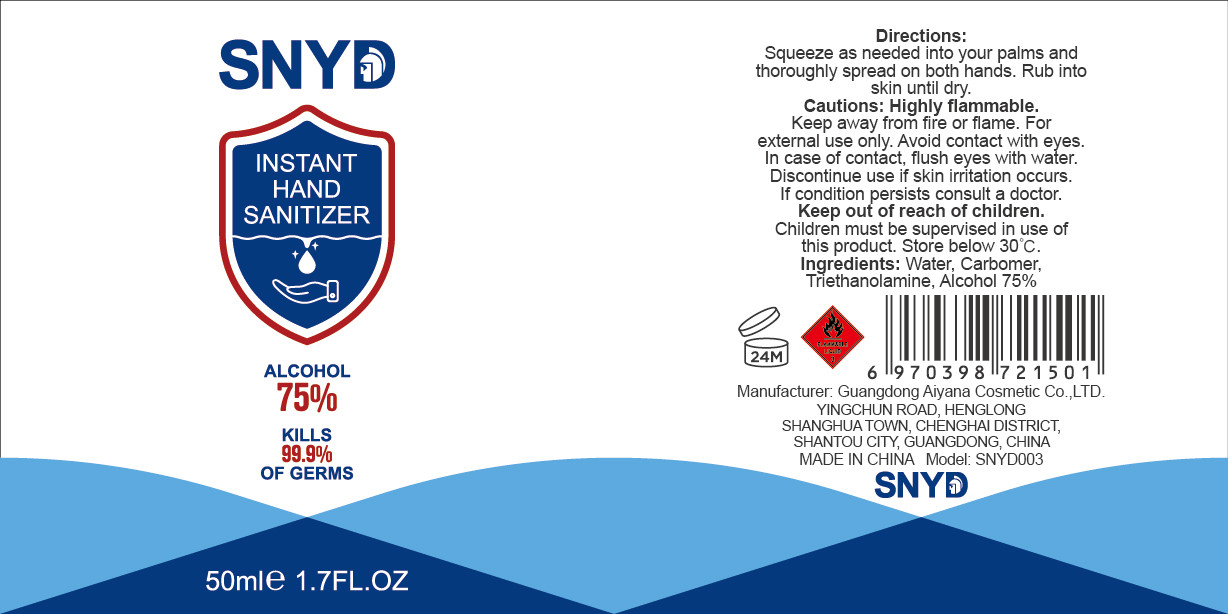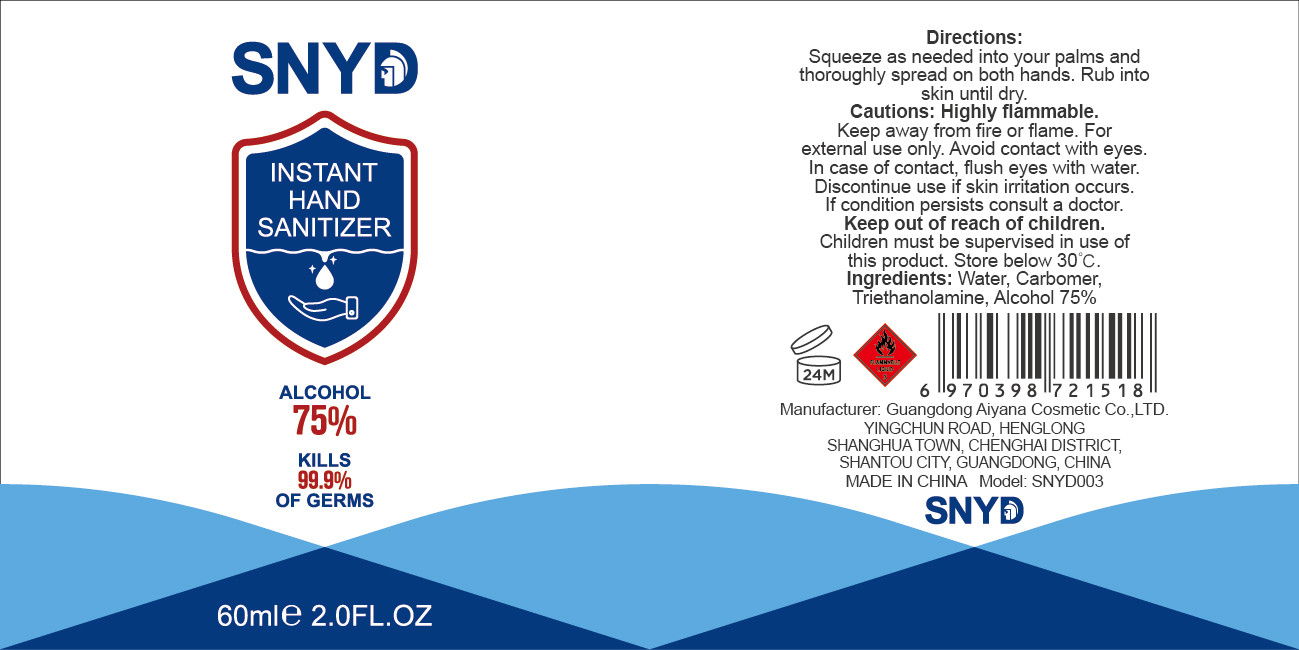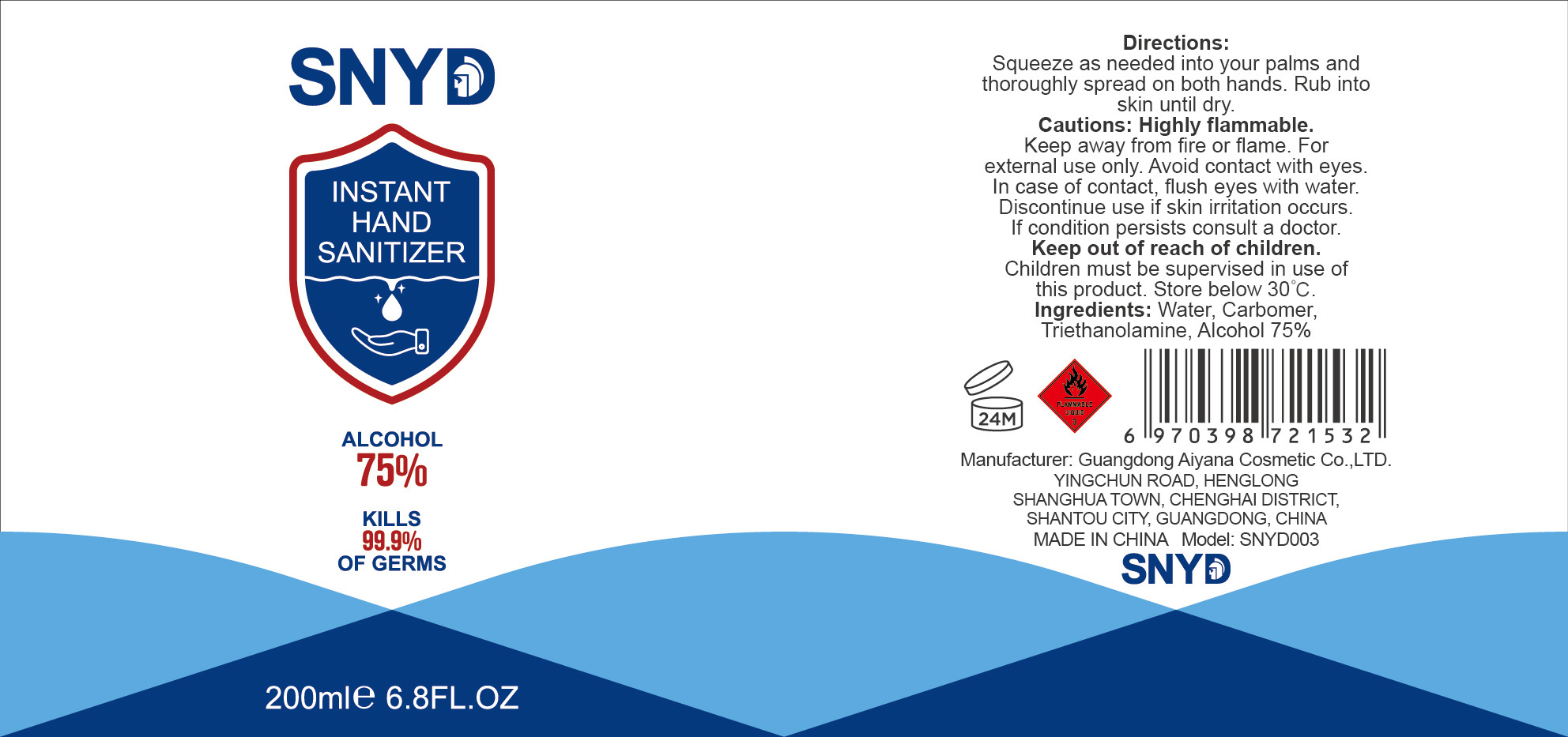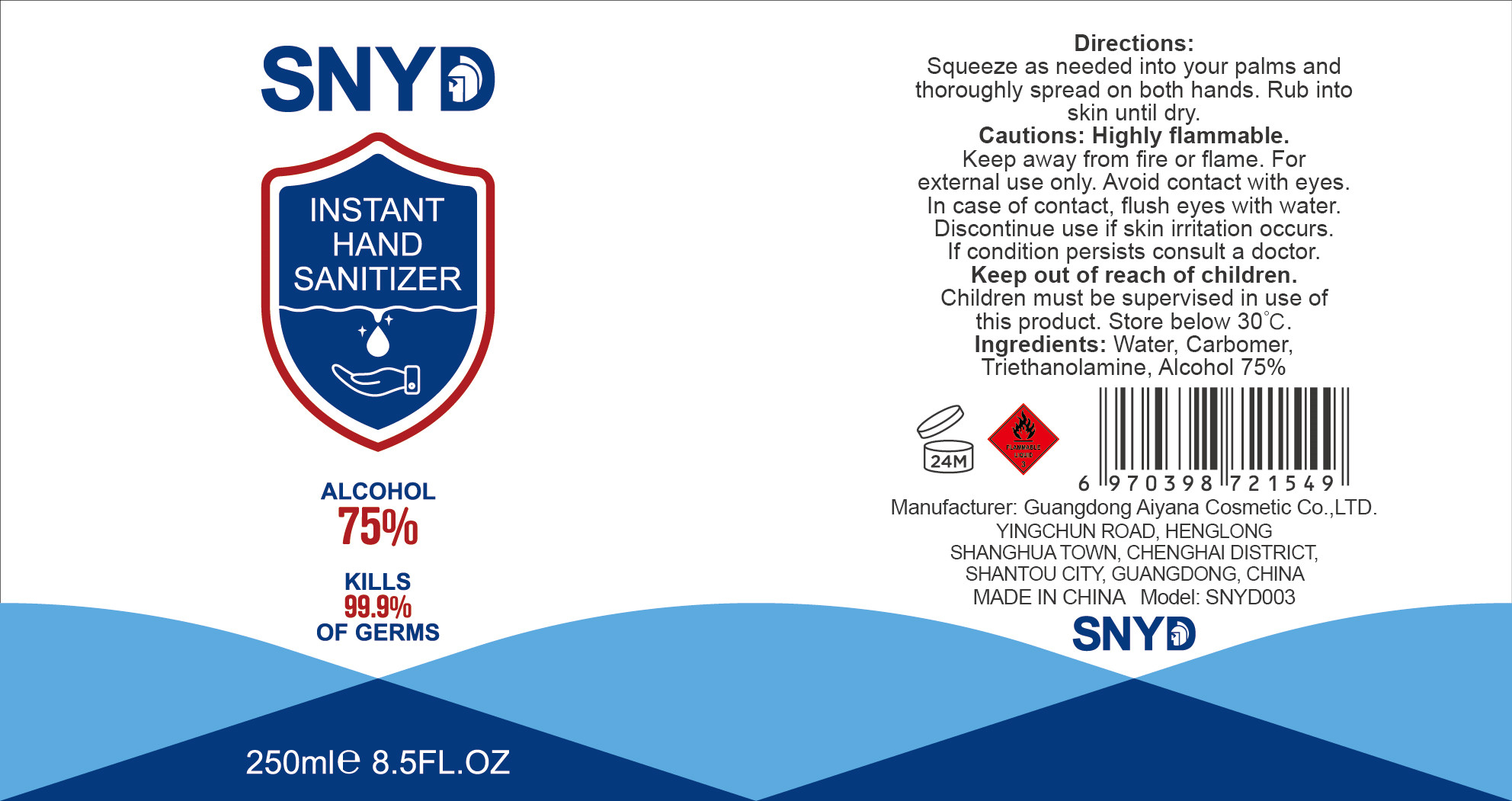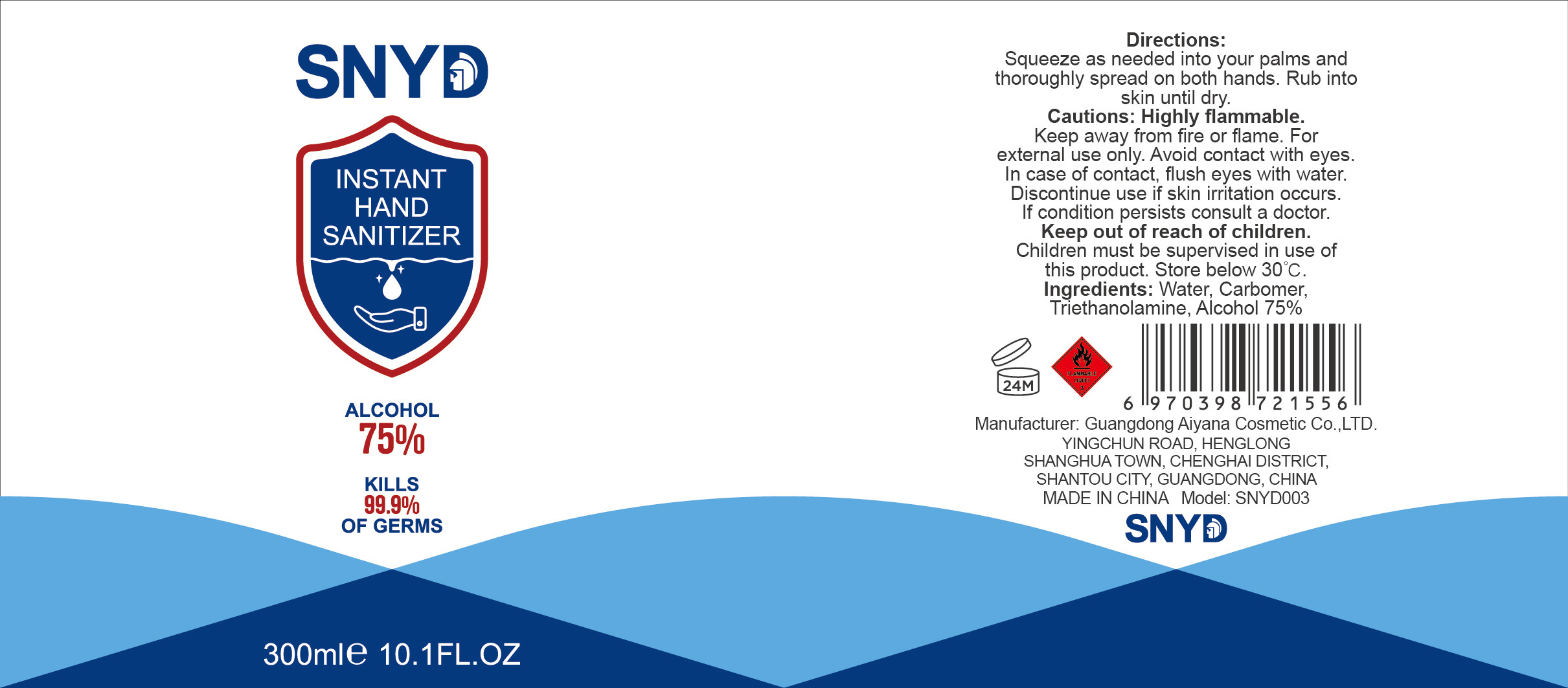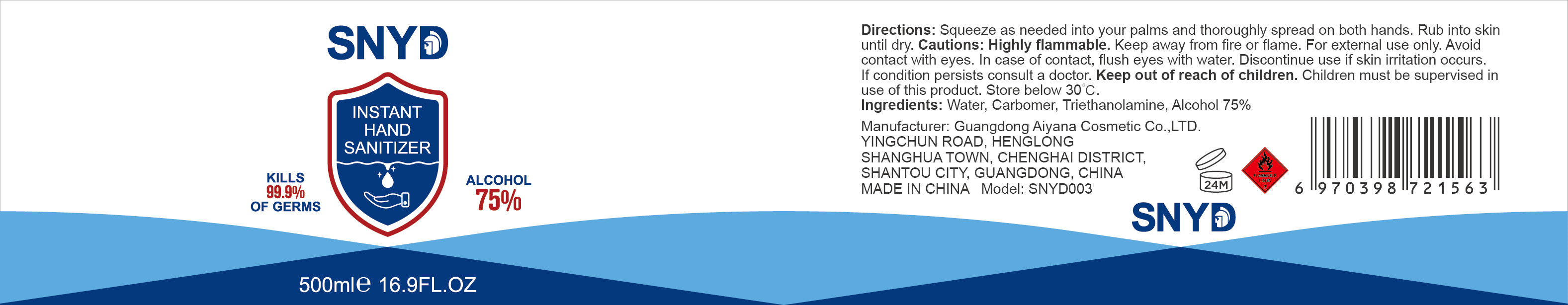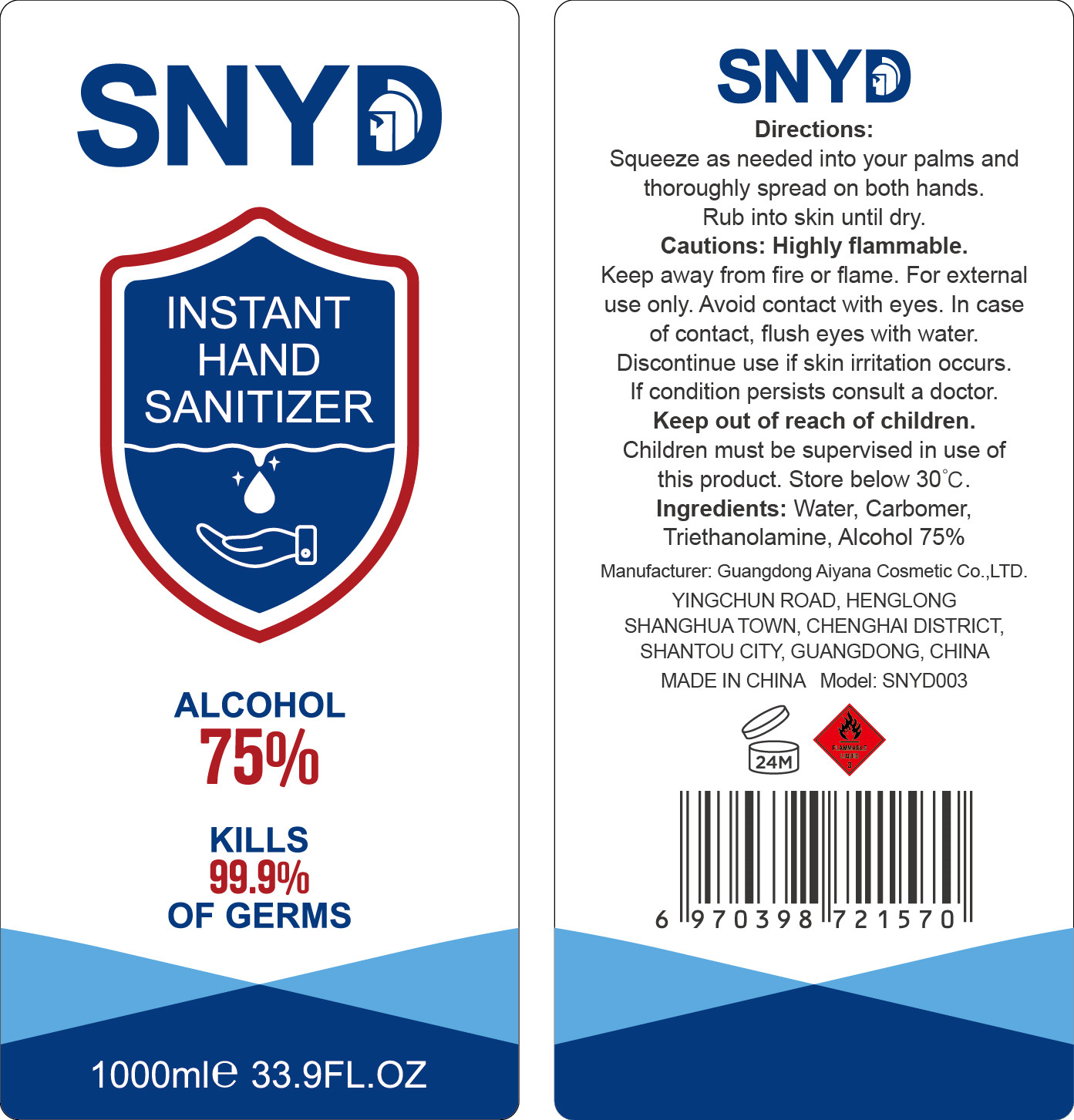 DRUG LABEL: Instant Hand Sanitizer
NDC: 41788-001 | Form: GEL
Manufacturer: Guangdong Aiyana Cosmetic Co., Ltd.
Category: otc | Type: HUMAN OTC DRUG LABEL
Date: 20200521

ACTIVE INGREDIENTS: ALCOHOL 75 mL/100 mL
INACTIVE INGREDIENTS: CARBOMER HOMOPOLYMER, UNSPECIFIED TYPE; WATER; TROLAMINE

DOSAGE AND ADMINISTRATION

Store below 30°C.

INACTIVE INGREDIENT

Water

Triethanolamine

Carbomer

INDICATIONS AND USAGE

Squeeze as needed into your palms and thoroughly spread on both hands. Rub into skin until dry.

ACTIVE INGREDIENT

Alcohol

keep out of reach of children

PURPOSE

Disinfection
Sterilization
No Rinseing

WARNINGS

Highly flammable.Keep away from fire or flame. For external use only. Avoid contact with eyes.In case of contact, flush eyes with water.Discontinue use if skin irritation occurs.If condition persists consult a doctor.Keep out of reach of children.Children must be supervised in use of this product. Store below 30°C.